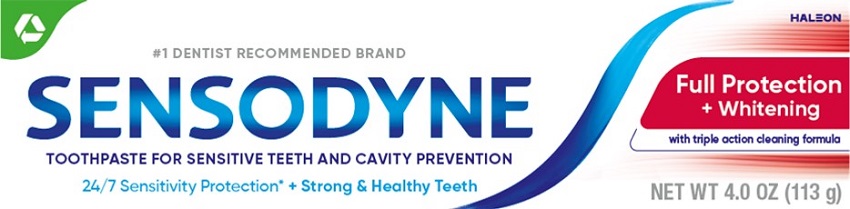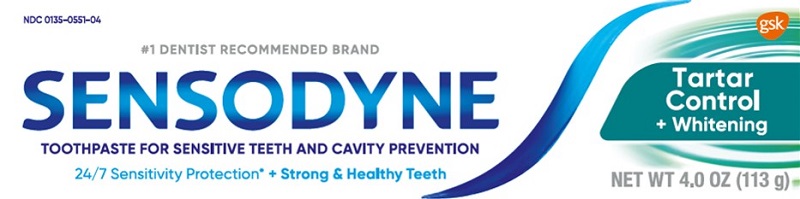 DRUG LABEL: Sensodyne
NDC: 0135-0550 | Form: PASTE
Manufacturer: Haleon US Holdings LLC
Category: otc | Type: HUMAN OTC DRUG LABEL
Date: 20240515

ACTIVE INGREDIENTS: POTASSIUM NITRATE 50 mg/1 g; SODIUM FLUORIDE 1.1 mg/1 g
INACTIVE INGREDIENTS: WATER; HYDRATED SILICA; SORBITOL; GLYCERIN; SODIUM TRIPOLYPHOSPHATE ANHYDROUS; POLYETHYLENE GLYCOL 400; TITANIUM DIOXIDE; COCAMIDOPROPYL BETAINE; SODIUM METHYL COCOYL TAURATE; XANTHAN GUM; SODIUM HYDROXIDE; SACCHARIN SODIUM; SUCRALOSE

Drug Facts

Active ingredients

Potassium nitrate 5%

Sodium fluoride 0.24% (0.15% w/v fluoride ion)

Purposes

Antihypersensitivity

Anticavity

Uses

- builds increasing protection against painful sensitivity of the teeth to cold, heat, acids, sweets, or contact.
- aids in the prevention of dental cavities.

Warnings

Stop use and ask a dentist if

- the problem persists or worsens. Sensitive teeth may indicate a serious problem that may need prompt care by a dentist.
- pain/sensitivity still persists after 4 weeks of use.

Keep out of reach of children.

If more than used for brushing is accidentally swallowed, get medical help or contact a Poison Control Center right away.

Directions

- adults and children 12 years of age and older:
  - apply at least a 1-inch strip of the product onto a soft bristle toothbrush.
  - brush teeth thoroughly for at least 1 minute twice a day (morning and evening), and not more than 3 times a day, or as recommended by a dentist or doctor. Make sure to brush all sensitive areas of the teeth. Minimize swallowing. Spit out after brushing.
- children under 12 years of age:Consult a dentist or doctor.

Other information

- do not store above 30°C (86°F)

Inactive ingredients

water, hydrated silica, sorbitol, glycerin, pentasodium triphosphate, PEG-8, flavor, titanium dioxide, sodium methyl cocoyl taurate, cocamidopropyl betaine, xanthan gum, sodium hydroxide, sodium saccharin, sucralose

Questions or comments?

1-866-844-2797

Additional Information (Full Protection)

ALWAYS FOLLOW THE LABEL

What are sensitive teeth?

Lots of people hove sensitive teeth. When enamel is worn away (through eating everyday acidic food or drinks) or gums recede, the dentin underneath becomes exposed. This can lead to tooth sensitivity, for example, with cold and hot food and drinks.

What does Sensodyne do?

Sensodyne provides daily care for sensitive teeth* plus all the benefits you would expect from a daily

fluoride toothpaste - strong teeth and freshness.

*with twice daily brushing.

Exposed Dentin

24/7 Sensitivity Protection*

+ Strong & Healthy Teeth

Use Sensodyne Full Protection

+ Whitening twice daily:

- Long lasting sensitivity protection* every day
- Contains fluoride to protect against cavities

Trademarks are owned by or licensed to the GSK group of companies.

©2020 GSK group of companies or its licensor.

Distributed by:

GSK Consumer Healthcare

Warren, NJ 07059

Additional Information (Tartar Control)

Use Sensodyne Tartar Control

+ Whitening twice daily:

- Long lasting sensitivity protection* every day
- Contains fluoride to protect against cavities

Principal Display Panel

#1 DENTIST RECOMMENDED BRAND HALEON

SENSODYNE

TOOTHPASTE FOR SENSITIVE TEETH AND CAVITY PREVENTION

24/7 SENSITIVITY PROTECTION* + Strong & Healthy Teeth

Full Protection + Whitening

with triple action cleaning formula

NET WT 4.0 OZ (113 g)

62000000208034

Principal Display Panel

NDC 0135-0551-04

#1 DENTIST RECOMMENDED BRAND

SENSODYNE

TOOTHPASTE FOR SENSITIVE TEETH AND CAVITY PREVENTION

24/7 SENSITIVITY PROTECTION* + Strong & Healthy Teeth

Tartar Control + Whitening

NET WT 4.0 OZ (113 g)

62000000053367